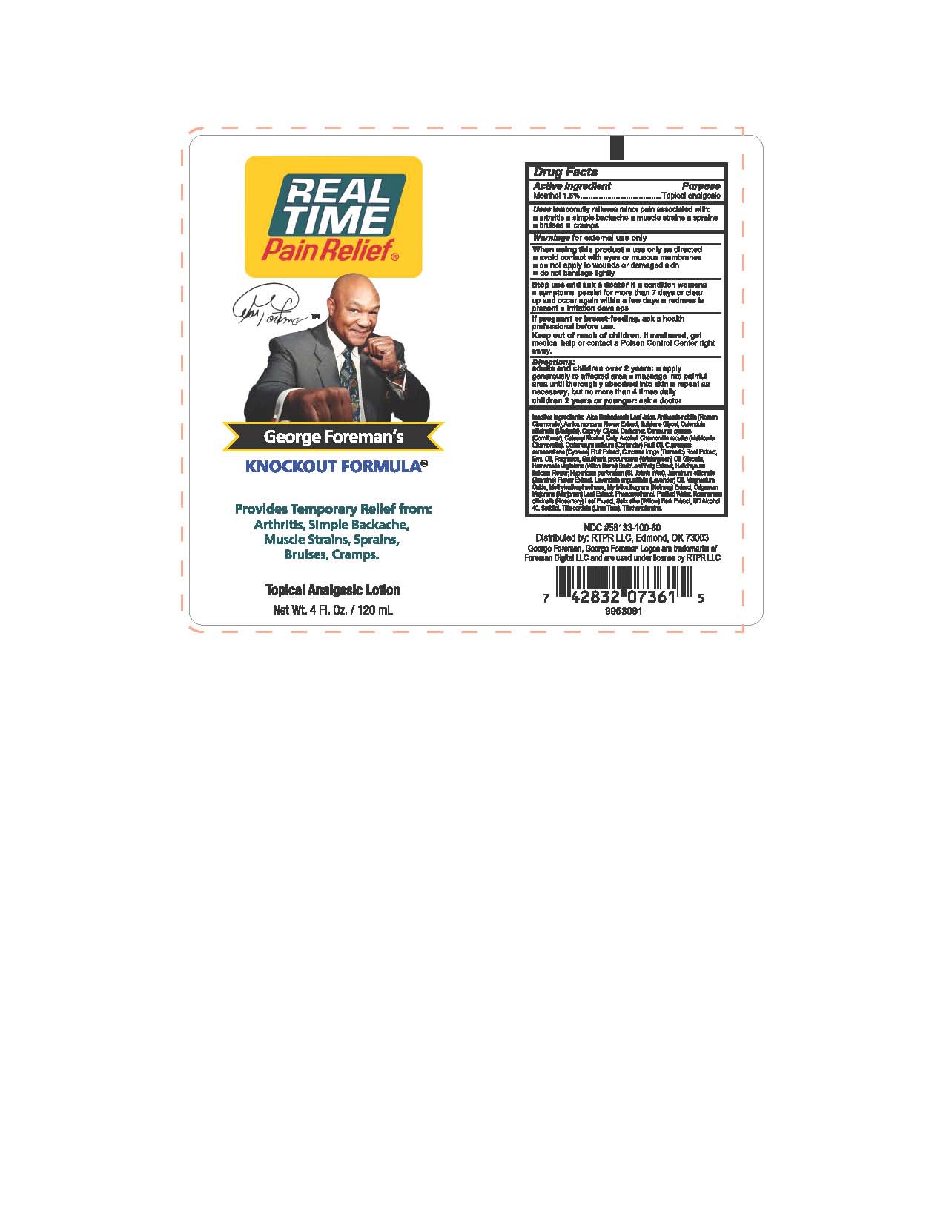 DRUG LABEL: Real Time Pain Relief MAXX
NDC: 58133-100 | Form: LOTION
Manufacturer: Cosmetic Specialty Labs, Inc.
Category: otc | Type: HUMAN OTC DRUG LABEL
Date: 20200210

ACTIVE INGREDIENTS: MENTHOL 1.5 g/100 mL
INACTIVE INGREDIENTS: DIMETHYL SULFONE; HYPERICUM PERFORATUM FLOWER; CAPRYLYL GLYCOL; TRIETHANOLAMINE TRIS(DIHYDROGEN PHOSPHATE); ALOE VERA LEAF; CHAMAEMELUM NOBILE FLOWER; ARNICA MONTANA FLOWER; CALENDULA OFFICINALIS FLOWER; CAPSICUM; CARBOMER HOMOPOLYMER TYPE B (ALLYL SUCROSE CROSSLINKED); CENTAUREA CYANUS FLOWER; CETOSTEARYL ALCOHOL; CETYL ALCOHOL; CORIANDER OIL; DIAZOLIDINYL UREA; EMU OIL; GLUCOSAMINE HYDROCHLORIDE; HAMAMELIS VIRGINIANA TOP; PHENOXYETHANOL; WATER; SALIX ALBA BARK; ISOPROPYL ALCOHOL; SODIUM CHONDROITIN SULFATE (PORCINE; 5500 MW); SORBITOL; TILIA X EUROPAEA FLOWER; BUTYLENE GLYCOL; MENTHA PIPERITA LEAF; ANTHEMIS ARVENSIS FLOWERING TOP

Real Time Pain Relief George Foreman Knockout Formula

Drug Facts

Active Ingredient

Menthol 1.5%

Purpose

Topical analgesic

Uses

temporarily relieves minor pain associated with:

- arthritis
- simple backache
- muscle strains
- sprains
- bruises
- cramps

Warnings

for external use only

When using this product

- use only as directed
- avoid contact with eyes or mucous membranes
- do not apply to wounds or damaged skin
- do not bandage tightly

Stop use and ask a doctor if

- condition worsens
- symptoms persist for more than 7 days or clear up and occur again within a few days
- redness is present
- irritation develops

PREGNANCY OR BREAST FEEDING

If pregnant or breast-feeding, ask a health professional before use.

Keep out of reach of children. If swallowed, get medical help or contact a Poison Control Center right away.

Directions

adults and children over 2 years:

- apply generously to affected area
- massage into painful area until thoroughly absorbed into skin
- repeat as necessary, but no more than 4 times daily

children 2 years or younger: ask a doctor

Inactive ingredients

Aloe Barbadensis Leaf, Anthemis nobilis, Arnica Montana Flower Extract, Butylene Glycol, Calendula officianlis, Caprylyl Glycol, Capsicum Frutescens Fruit, Carbomer, Centaurea cyanus, Cetearyl Alcohol, Cetyl Alcohol, Coriandrum Sativum (Coriander) Fruit Oil, Diazolidinyl Urea, Emu Oil, Glucosamine HCI, Hamamelis Virginiana (Witch Hazel) Bark/Leaf/Twig Extract, Hypericum perforatum, Matricaria chamomilla, Mentha Piperita (Peppermint) Leaf Oil, Methylsulfonylmethane, Phenoxyethanol, Purified Water, Salix Alba (Willow) Bark Extract, SD Alcohol 40, Sodium Chondroitin Sulfate, Sorbitol, Tilia cordata, Triethanolamine.

Distributed by: RTPR LLC, Edmond, OK 73012